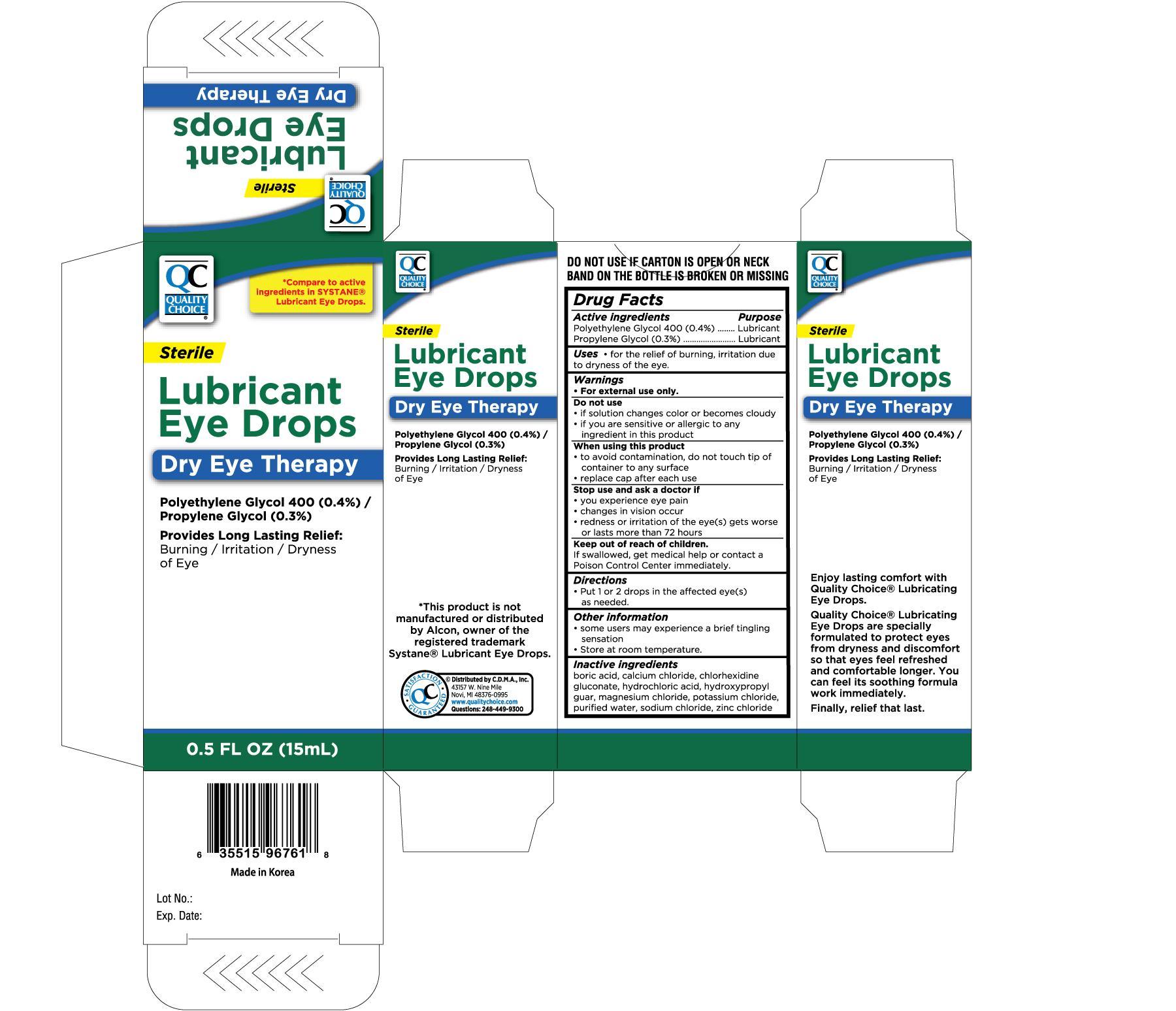 DRUG LABEL: QUALITY CHOICE LUBRICANT EYE
                
NDC: 63868-968 | Form: SOLUTION/ DROPS
Manufacturer: CHAIN DRUG MARKETING ASSOCIATION INC
Category: otc | Type: HUMAN OTC DRUG LABEL
Date: 20120930

ACTIVE INGREDIENTS: POLYETHYLENE GLYCOL 400 4 mg/1 mL; PROPYLENE GLYCOL 3 mg/1 mL
INACTIVE INGREDIENTS: BORIC ACID; CALCIUM CHLORIDE; CHLORHEXIDINE GLUCONATE; HYDROCHLORIC ACID; MAGNESIUM CHLORIDE; POTASSIUM CHLORIDE; SODIUM CHLORIDE; ZINC CHLORIDE; WATER

Drug Facts

Active ingredients Purpose

Polyethylene Glycol 400 (0.4%)..................................Lubricant

Propylene Glycol (0.3%).............................................Lubricant

Uses

For the relief of burning, irritation due to dryness of the eye.

Warnings

For external use only.

Do not use

- if solution changes color or becomes cloudy
- if you are sensitive or allergic to any ingredient in this product

When using this product

- to avoid contamination, do not touch tip of container to any surface
- replace cap after each use

Stop use and ask a doctor if

- you experience eye pain
- changes in vision occur
- redness or irritation of the eye(s) gets worse or lasts more than 72 hours

Keep out of reach of children.

If swallowed, get medical help or contact a Poison Control Center immediately.

Directions

- Put 1 or 2 drops in the affected eye(s) as needed.

Other information

- some users may experience a brief tingling sensation
- Store at room temperature

INACTIVE INGREDIENT

Inactive ingredients: Boric Acid, Calcium Chloride, Chlorhexidine Gluconate, Hydrochloric Acid, Hydroxypropyl Guar,

Magnesium Chloride, Potassium Chloride, Purified Water, Sodium Chloride, Zinc Chloride

DOSAGE AND ADMINISTRATION

Distributed by C.D.M.A., Inc.

43157 W. Nine Mile

Novi, MI 48376-0995

www.qualitychoice.com

Made in Korea